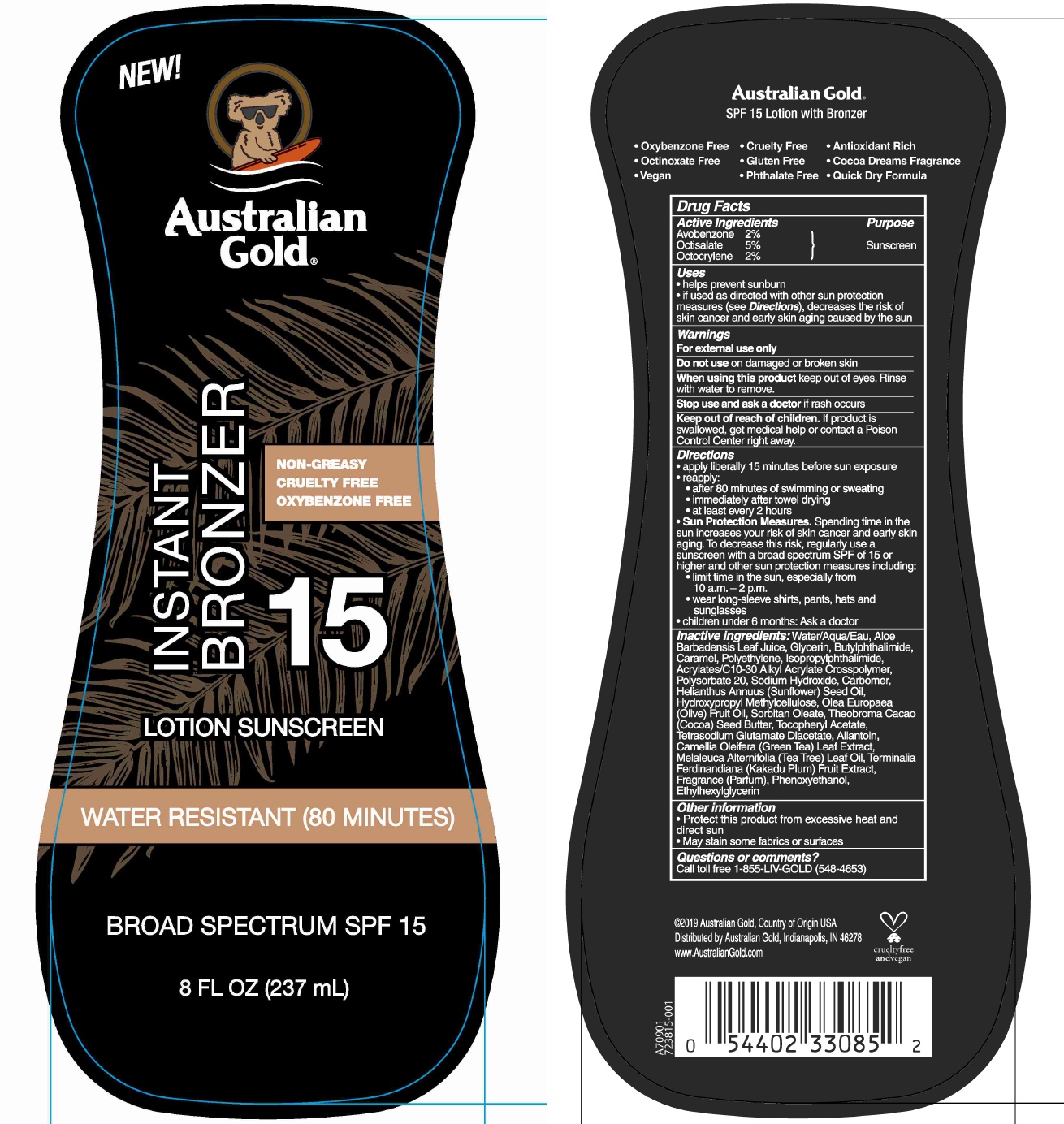 DRUG LABEL: Australian Gold
NDC: 58443-0280 | Form: LOTION
Manufacturer: Prime Enterprises Inc.
Category: otc | Type: HUMAN OTC DRUG LABEL
Date: 20210112

ACTIVE INGREDIENTS: AVOBENZONE 20.36 mg/1 mL; OCTISALATE 50.9 mg/1 mL; OCTOCRYLENE 20.36 mg/1 mL
INACTIVE INGREDIENTS: N-BUTYLPHTHALIMIDE; ISOPROPYLPHTHALIMIDE; KAKADU PLUM; .ALPHA.-TOCOPHEROL ACETATE; CARBOMER INTERPOLYMER TYPE A (55000 CPS); ALLANTOIN; TEA TREE OIL; POLYSORBATE 20; ALOE VERA LEAF; CAMELLIA OLEIFERA LEAF; CARAMEL; CARBOMER 980; ETHYLHEXYLGLYCERIN; GLYCERIN; SUNFLOWER OIL; HYPROMELLOSES; WATER; OLIVE OIL; HIGH DENSITY POLYETHYLENE; SORBITAN MONOOLEATE; TETRASODIUM GLUTAMATE DIACETATE; SODIUM HYDROXIDE; PHENOXYETHANOL; COCOA BUTTER

Australian Gold Instant Bronzer 15 Lotion Sunscreen

Active Ingredients

Avobenzone 2%

Octisalate 5%

Octocrylene 2%

Purpose

Sunscreen

Uses

• helps prevent sunburn

• if used as directed with other sun protection measures (see Directions), decreases the risk of skin cancer and early skin aging caused by the sun.

Warnings

For external use only

Do not use on damaged or broken skin.

When using this product keep out of eyes. Rinse with water to remove.

Stop use and ask a doctor if rash occurs.

Keep out of reach of children. If product is swallowed, get medical help or contact a Poison Control Center right away.

Directions

- apply liberally 15 minutes before sun exposure
- reapply:
- after 80 minutes of swimming or sweating
- immediately after towel drying
- at least every 2 hours
- Sun Protection Measures. Spending time in the sun increases your risk of skin cancer and early skin aging. To decrease this risk, regularly use a sunscreen with broad spectrum SPF of 15 or higher and other sun protection measures including:
- limit time in the sun, especially from 10 a.m. – 2 p.m.
- wear long-sleeved shirts, pants, hats, & sunglasses.
- Children under 6 months: Ask a doctor

Inactive Ingredients

Water/Aqua/Eau, Aloe Barbadensis Leaf Juice, Glycerin, Butylphthalimide, Caramel, Polyethylene, Isopropylphthalimide, Acrylates/C10-30 Alkyl Acrylate Crosspolymer, Polysorbate 20, Sodium Hydroxide, Carbomer, Helianthus Annuus (Sunflower) Seed Oil, Hydroxypropyl Methylcellulose, Olea Europaea (Olive) Fruit Oil, Sorbitan Oleate, Theobroma Cacao (Cocoa) Seed Butter, Tocopheryl Acetate, Tetrasodium Glutamate Diacetate, Allantoin, Camellia Oleifera (Green Tea) Leaf Extract, Melaleuca Alternifolia (Tea Tree) Leaf Oil, Terminalia Ferdinandiana (Kakadu Plum) Fruit Extract, Fragrance(Parfum), Phenoxyethanol, Ethylhexylglycerin

Other information

- Protect this product from excessive heat and direct sun
- May stain some fabrics or surfaces

Questions or comments?

Call toll free 1-855-LIV-GOLD (548-4653)